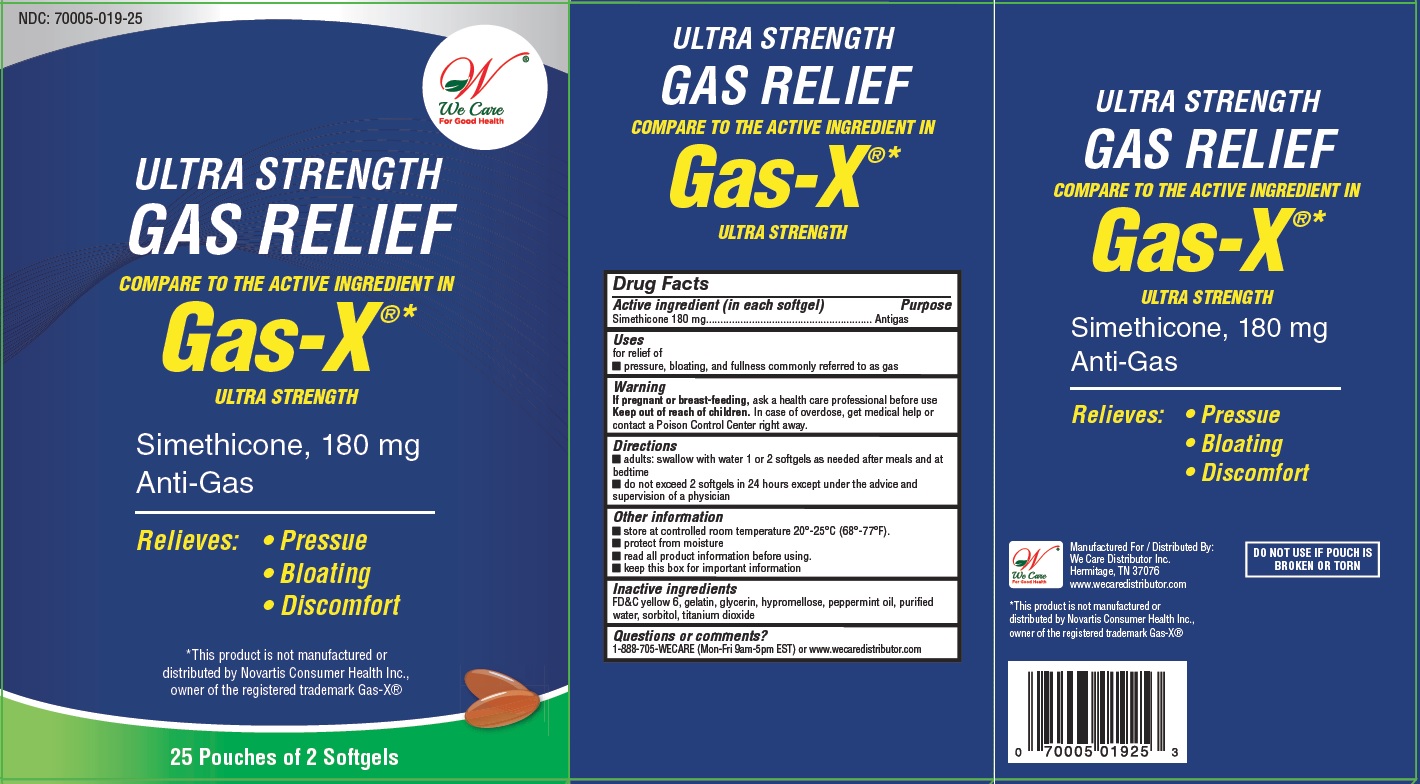 DRUG LABEL: Gas Relief
NDC: 70005-019 | Form: CAPSULE, LIQUID FILLED
Manufacturer: We Care Distributor Inc.
Category: otc | Type: HUMAN OTC DRUG LABEL
Date: 20160322

ACTIVE INGREDIENTS: DIMETHICONE 180 mg/1 1
INACTIVE INGREDIENTS: FD&C YELLOW NO. 6; GELATIN; GLYCERIN; HYPROMELLOSES; PEPPERMINT OIL; WATER; SORBITOL; TITANIUM DIOXIDE

Gas Relief - Simethicone 180 mg

Drug Facts

ACTIVE INGREDIENT

Active ingredient (in each softgel) Purpose

Simethicone 180 mg............................................................. Antigas

Uses

for relief of

■ pressure, bloating, and fullness commonly referred to as gas

Warnings

If pregnant or breast-feeding,

ask a health care professional before use

Keep out of reach of children.

In case of overdose, get medical help or contact a Poison Control Center right away.

Directions

■ adults: swallow with water 1 or 2 softgels as needed after meals and at bedtime

■ do not exceed 2 softgels in 24 hours except under the advice and supervision of a physician

Other information

■ store at controlled room temperature 20°-25°C (68°-77°F).

■ protect from moisture

■ read all product information before using.

■ keep this box for important information

Inactive ingredients

FD&C yellow 6, gelatin, glycerin, hypromellose, peppermint oil, purified water, sorbitol, titanium dioxide

Questions or comments?

1-888-705-WECARE (Mon-Fri 9am-5pm EST) or www.wecaredistributor.com

PRINCIPAL DISPLAY PANEL

Compare to the Active Ingredients in
Gas-X Ultra Strength

Simethicone Softgels, 80 mg

TO OPEN
PUSH IN TAB AND PULL OUT

25 Pouches of 2 Softgel Each